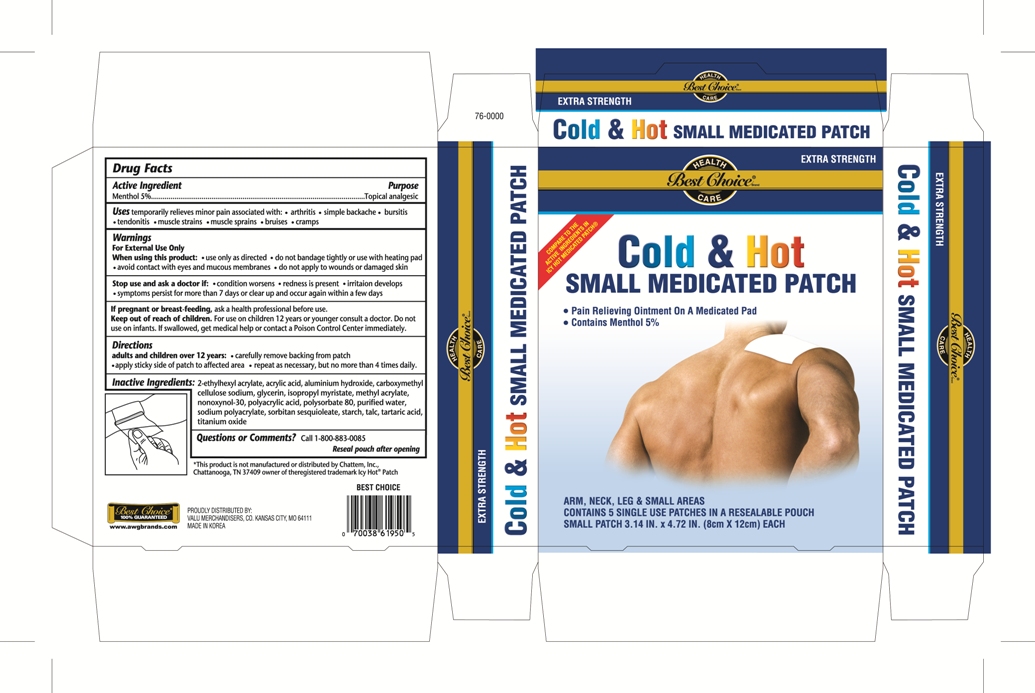 DRUG LABEL: Cold and Hot Medicated Pain Relief Small
NDC: 63941-950 | Form: PATCH
Manufacturer: Valu Merchandisers Company, Inc.
Category: otc | Type: HUMAN OTC DRUG LABEL
Date: 20110912

ACTIVE INGREDIENTS: MENTHOL 400 mg/1 1
INACTIVE INGREDIENTS: ACRYLIC ACID; ALUMINUM HYDROXIDE; CARBOXYMETHYLCELLULOSE SODIUM; GLYCERIN; ISOPROPYL MYRISTATE; METHYL ACRYLATE; NONOXYNOL-30; POLYSORBATE 80; WATER; SORBITAN SESQUIOLEATE; TALC; TARTARIC ACID; TITANIUM DIOXIDE

Drug Facts

Active Ingredient

Menthol 5%

Purpose

Topical analgesic

Uses

Temporarily relieves minor pain associated with:

- arthritis
- simple backache
- bursitis
- tendonitis
- muscle strains
- muscle sprains
- bruises
- cramps

Warnings

For external use only

When using this product

- use only as directed
- do not bandage tightly or use with heating pad
- avoid contact with eyes and mucous membranes
- do not apply to wounds or damaged skin

Stop use and ask a doctor if

- condition worsens
- redness is present
- irritation develops
- symptoms persist for more than 7 days or clear up and occur again within a few days

If pregnant or breast-feeding,

ask a health professional before use.

Keep out of reach of children.

For use on children 12 years or younger consult a doctor. Do not use on infants. If swallowed, get medical help or contact a Poison Control Center immediately.

Directions

Adults and children over 12 years:

- carefully remove backing from patch
- apply sticky side of patch to affected area
- repeat as necessary, but no more than 4 times daily

Inactive ingredients

2-ethylhexyl acrylate, acrylic acid, aluminium hydroxide, carboxymethylcellulose sodium, glycerin, isopropyl myristate, methyl acrylate, nonoxynol-30, polyacrylic acid, polysorbate 80, purified water, sodium polyacrylate, sorbitan sesquioleate, starch, talc, tartaric acid, titanium oxide

package label

Best Choice Cold and Hot Small Medicated Patch